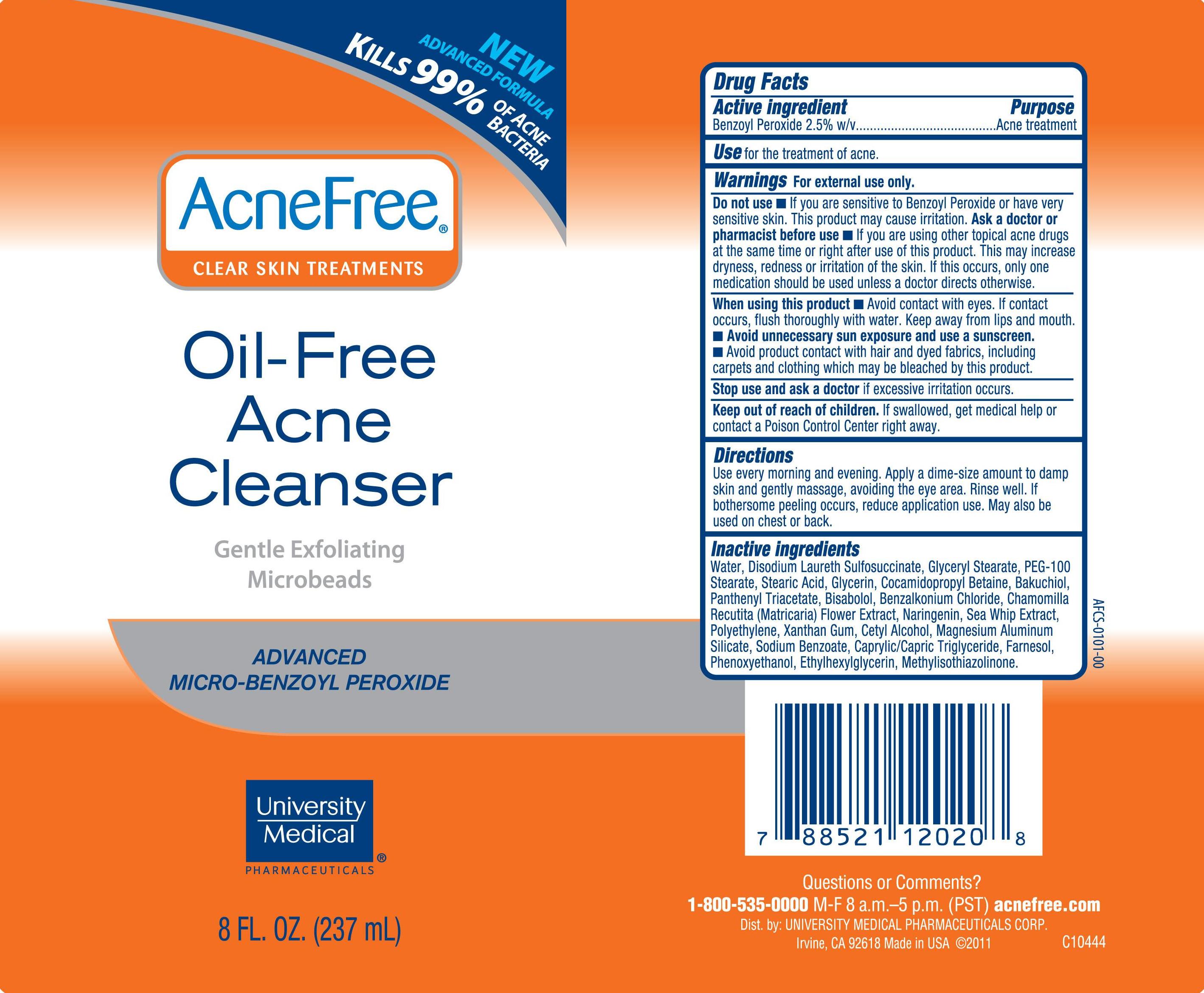 DRUG LABEL: Oil-Free Acne Cleanser
NDC: 50544-001 | Form: CREAM
Manufacturer: University Medical Pharmaceuticals Corp
Category: otc | Type: HUMAN OTC DRUG LABEL
Date: 20111101

ACTIVE INGREDIENTS: Benzoyl Peroxide 2.5 g/100 g
INACTIVE INGREDIENTS: water; DISODIUM LAURETH SULFOSUCCINATE; GLYCERYL MONOSTEARATE; PEG-100 STEARATE; STEARIC ACID; glycerin; COCAMIDOPROPYL BETAINE; MATRICARIA RECUTITA; LEVOMENOL; BENZALKONIUM CHLORIDE; PSEUDOPTEROGORGIA ELISABETHAE; HIGH DENSITY POLYETHYLENE; MAGNESIUM ALUMINUM SILICATE; MEDIUM-CHAIN TRIGLYCERIDES; XANTHAN GUM; CETYL ALCOHOL; CETYL ESTERS WAX; SODIUM BENZOATE; PHENOXYETHANOL; ETHYLHEXYLGLYCERIN; METHYLISOTHIAZOLINONE

Oil-Free Acne Cleanser

Active Ingredient: Benzoyl Peroxide 2.5% w/v

Purpose: Acne Treatment

INDICATIONS AND USAGE

Use for the treatment of acne.

Warnings For external use only.

Do not use: If you are sensitive to Benzoyl Peroxide or have very sensitive skin. This product may cause irritation.

Ask a doctor or pharmacist before use: If you are using other topical acne drugs at the same time or right before use of this product. This may increase dryness, redness or irritation of the skin. If this occurs, only one medication should be used unless a doctor directs otherwise.

When using this product:

- Avoid contact with eyes. If contact occurs, flush thoroughly with water. Keep away from lips and mouth.
- Avoid unnecessary sun exposure and use a sunscreen.
- Avoid product with hair and dyed fabrics, including carpets and clothing which may be bleached by this product.

Stop use and ask a doctor: If excessive irritation occurs.

Keep out of reach of children: If swallowed, get medical help or contact a Poison Control Center right away.

DOSAGE AND ADMINISTRATION

Directions: Use every morning and evening. Apply a dime-size amount to damp skin and gently massage, avoiding the eye area. Rinse well. If bothersome peeling occurs, reduce application use. May also be used on chest or back.

INACTIVE INGREDIENT

Inactive ingredients: Water, Disodium Laureth Sulfosuccinate, Glyceryl Stearate, PEG-100 Stearate, Stearic Acid, Glycerin, Cocamidopropyl Betaine, Bakuchiol, Panthenyl Triacetate, Bisabolol, Benzalkonium Chloride, Chamomilla Recuita (Matricaria) Flower Extract, Naringenin, Sea Whip Extract, Polyethylene, Xanthan Gum, Cetyl Alcohol, Magnesium Aluminum Silicate, Sodium Benzoate, Caprylic/Capric Triglyeride, Farnesol, Phenoxyethanol, Ethylhexylglycerin, Methylisothiazolinone.

PACKAGE LABEL

AcneFree Clear Skin Treatments
Oil-Free Acne Cleanser
Gentle Exfoliating Microbeads
Advanced Micro-Benzoyl Peroxide